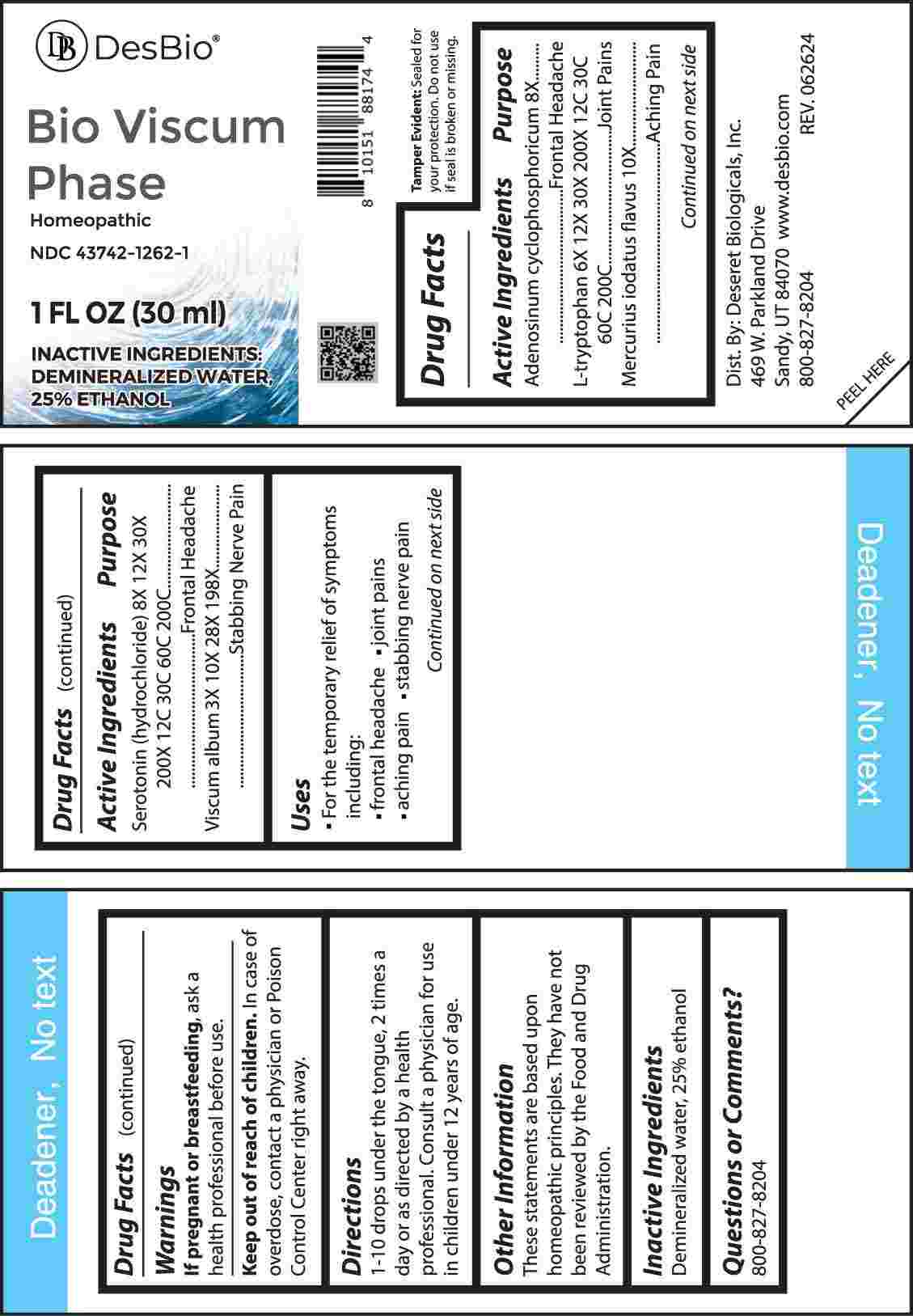 DRUG LABEL: Bio Viscum Phase
NDC: 43742-1262 | Form: LIQUID
Manufacturer: Deseret Biologicals, Inc.
Category: homeopathic | Type: HUMAN OTC DRUG LABEL
Date: 20241023

ACTIVE INGREDIENTS: VISCUM ALBUM FRUITING TOP 3 [hp_X]/1 mL; SEROTONIN HYDROCHLORIDE 6 [hp_X]/1 mL; TRYPTOPHAN 8 [hp_X]/1 mL; ADENOSINE CYCLIC PHOSPHATE 8 [hp_X]/1 mL; MERCUROUS IODIDE 10 [hp_X]/1 mL
INACTIVE INGREDIENTS: WATER; ALCOHOL

DRUG FACTS:

ACTIVE INGREDIENTS:

Adenosinum Cyclophosphoricum 8X, L-Tryptophan 6X, 12X, 30X, 200X, 12C, 30C, 60C, 200C, Mercurius Iodatus Flavus 10X, Serotonin (Hydrochloride) 8X, 12X, 30X, 200X, 12C, 60C, 200C, Viscum Album 3X, 10X, 28X, 198X.

PURPOSE:

Adenosinum Cyclophosphoricum – Frontal Headache, L-Tryptophan – Joint Pains, Mercurius Iodatus Flavus – Aching Pain, Serotonin (Hydrochloride) – Frontal Headache, Viscum Album – Stabbing Nerve Pain

USES:

• For the temporary relief of symptoms including:

• frontal headaches • joint pain • aching pain • stabbing nerve pain

These statements are based upon homeopathic principles. They have not been reviewed by the Food and Drug Administration.

WARNINGS:

If pregnant or breast-feeding, ask a health professional before use.

Keep out of reach of children. In case of overdose, contact a physician or Poison Control Center right away.

Tamper Evident: Sealed for your protection. Do not use if seal is broken or missing.

KEEP OUT OF REACH OF CHILDREN:

In case of overdose, contact a physician or Poison Control Center right away.

DIRECTIONS:

1-10 drops under the tongue, 2 times a day or as directed by a health professional. Consult a physician for use in children under 12 years of age.

INACTIVE INGREDIENTS:

Demineralized water, 25% ethanol

QUESTIONS:

Dist. By: Deseret Biologicals, Inc.

469 W. Parkland Drive

Sandy, UT 84070

www.desbio.com

800-827-8204

PACKAGE LABEL DISPLAY:

DesBio

Bio Viscum Phase

Homeopathic

NDC 43742-1262-1

1 FL OZ (30 ml)